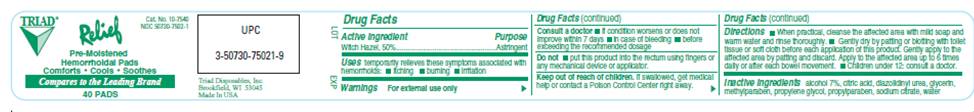 DRUG LABEL: Relief
NDC: 50730-7502 | Form: SWAB
Manufacturer: H and P Industries, Inc. dba Triad Group
Category: otc | Type: HUMAN OTC DRUG LABEL
Date: 20091123

ACTIVE INGREDIENTS: witch hazel .5 mL/1 1
INACTIVE INGREDIENTS: citric acid monohydrate; diazolidinylurea; glycerin; methylparaben; propylene glycol; propylparaben; sodium citrate; water

DRUG FACTS

ACTIVE INGREDIENT

Witch Hazel 50%

PURPOSE

Astringent

USES

Temporarily relieves these symptoms associated with hemorrhoids:

- itching
- burning
- irritation

WARNINGS

For external use only.

Stop use and ask a doctor

- if condition worsens or does not improve within 7 days
- in case of bleeding
- before exceeding the recommended dosage

Do not

put this product into rectum using fingers or any mechanical device or applicator

Keep out of reach of children

If swallowed, get medical help or contact a Poison Control Center right away.

DIRECTIONS

- When practical, cleanse the affected area with mild soap and warm water and rinse thoroughly.
- Gently dry by patting or blotting with toilet tissue or soft cloth before each application of this product. Gently apply to the affected area by patting and then discard. Apply to the affected area up to 6 times daily or after each bowel movement.
- Children under 12 years of age: consult a doctor.

Inactive ingredients

citric acid, diazolidinyl urea, glycerin, methylparaben, propylene glycol, propylparaben, sodium citrate, water

Package Information

CAT. NO. 10-7540
NDC 50730-7502-1
Relief
Pre-Moistened
Hemorrhoidal Pads
Comforts - Cools - Soothes
Compares to the leading brand
40 PADS
Triad Disposables, Inc.
Brookfield, WI 53045
Made In USA